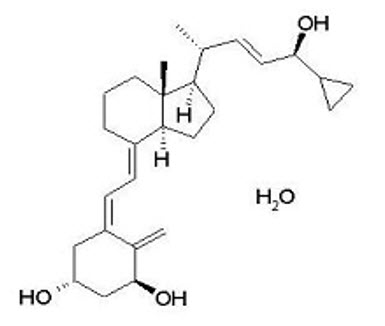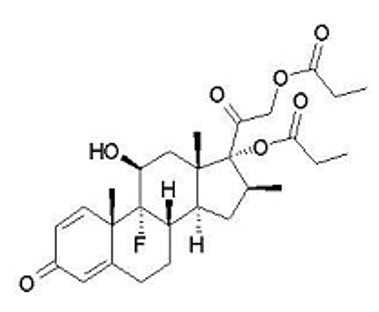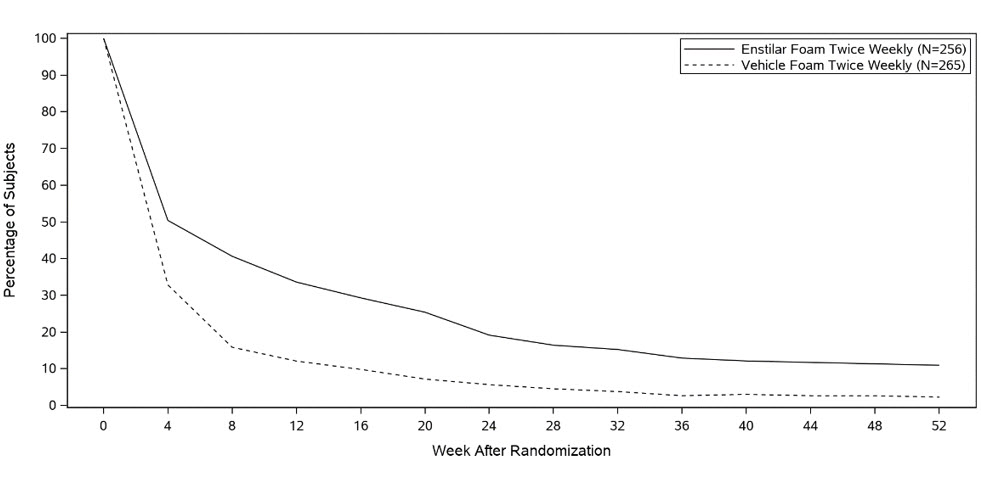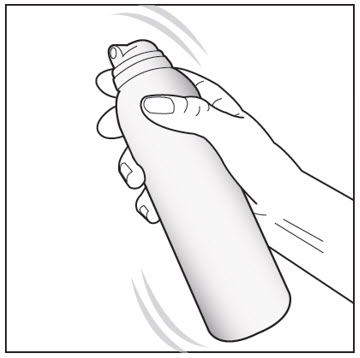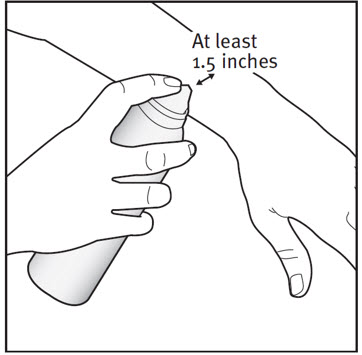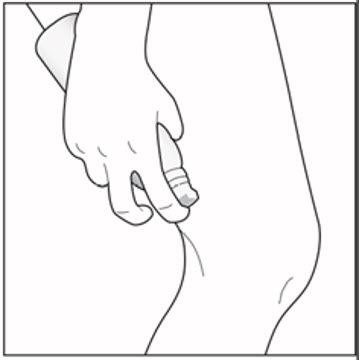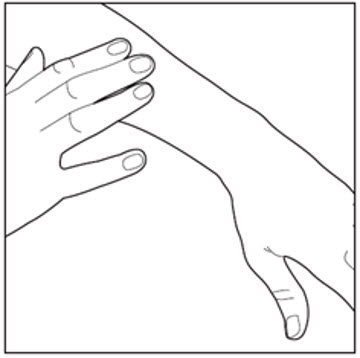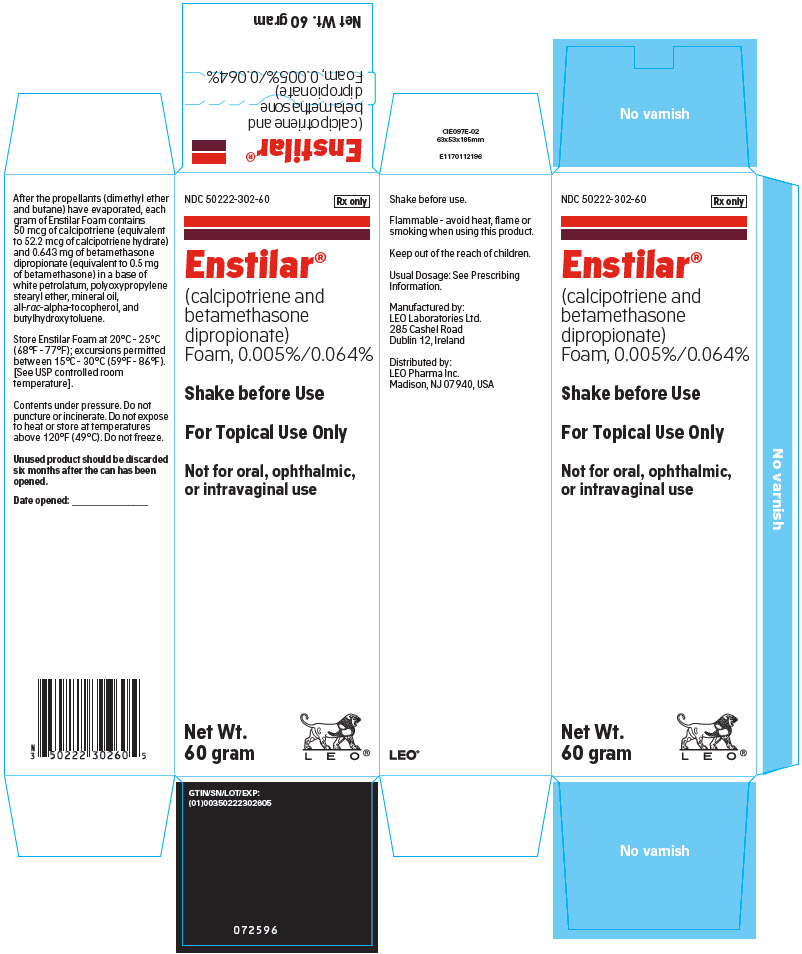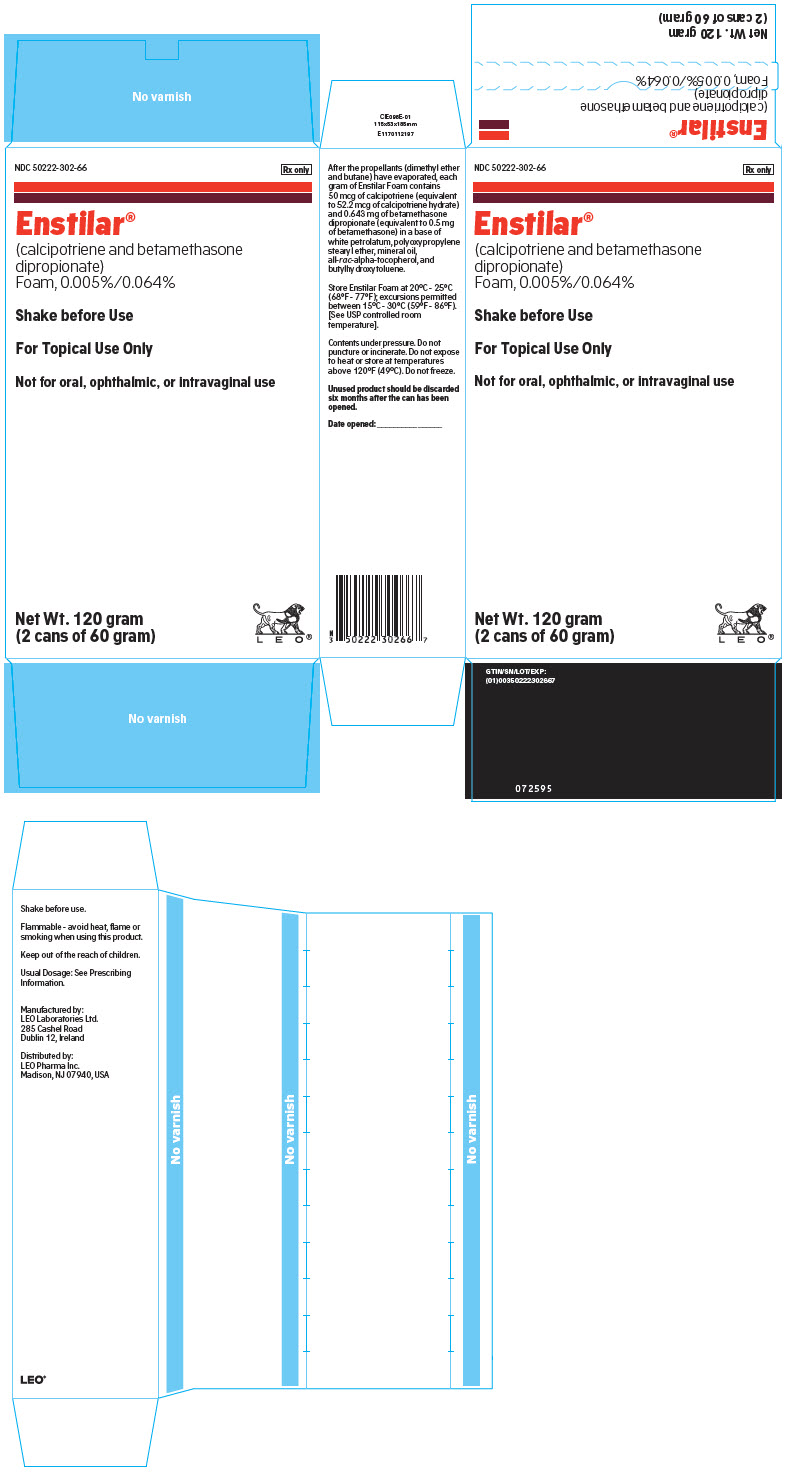 DRUG LABEL: ENSTILAR
NDC: 50222-302 | Form: AEROSOL, FOAM
Manufacturer: LEO Pharma Inc.
Category: prescription | Type: HUMAN PRESCRIPTION DRUG LABEL
Date: 20211018

ACTIVE INGREDIENTS: CALCIPOTRIENE MONOHYDRATE 50 ug/1 g; BETAMETHASONE DIPROPIONATE 0.5 mg/1 g
INACTIVE INGREDIENTS: PETROLATUM; BUTANE; DIMETHYL ETHER; POLYPROPYLENE GLYCOL 11 STEARYL ETHER; MINERAL OIL; .ALPHA.-TOCOPHEROL, DL-; BUTYLATED HYDROXYTOLUENE

HIGHLIGHTS OF PRESCRIBING INFORMATION

These highlights do not include all the information needed to use ENSTILAR Foam safely and effectively. See full prescribing information for ENSTILAR Foam.
ENSTILAR® (calcipotriene and betamethasone dipropionate) foam, for topical use
Initial U.S. Approval: 2006

1 INDICATIONS AND USAGE

Enstilar Foam is a combination of calcipotriene, a vitamin D analog, and betamethasone dipropionate, a corticosteroid, indicated for the topical treatment of plaque psoriasis in patients 12 years and older. (1)

2 DOSAGE AND ADMINISTRATION

- Shake before use. Apply Enstilar Foam to affected area(s) once daily for up to 4 weeks. Discontinue therapy when control is achieved. Do not use more than 60 grams every 4 days. (2)
- Do not use with occlusive dressings unless directed by a healthcare provider. (2)
- Avoid use on the face, groin, or axillae, or if skin atrophy is present at the treatment site. (2)
- Not for oral, ophthalmic, or intravaginal use. (2)

3 DOSAGE FORMS AND STRENGTHS

Foam: 0.005%/0.064% - Each gram of Enstilar Foam contains 50 mcg of calcipotriene and 0.643 mg of betamethasone dipropionate. (3)

4 CONTRAINDICATIONS

None. (4)

5 WARNINGS AND PRECAUTIONS

- Flammability: The propellants in Enstilar Foam are flammable. Instruct the patient to avoid fire, flame, and smoking during and immediately following application. (5.1)
- Hypercalcemia and Hypercalciuria: Hypercalcemia and hypercalciuria have been observed with use of Enstilar Foam. If hypercalcemia or hypercalciuria develop, discontinue treatment until parameters of calcium metabolism have normalized. (5.2)
- Effects on Endocrine System: Topical corticosteroids can produce reversible hypothalamic-pituitary-adrenal (HPA) axis suppression with the potential for glucocorticosteroid insufficiency during and after withdrawal of treatment. Risk factors include the use of high-potency topical corticosteroids, use over a large surface area or on areas under occlusion, prolonged use, altered skin barrier, liver failure, and use in pediatric patients. Modify use should HPA axis suppression develop. (5.3, 8.4)
- Ophthalmic Adverse Reactions: Topical corticosteroid products may increase the risk of cataracts and glaucoma. If visual symptoms occur, consider referral to an ophthalmologist. (5.5)

6 ADVERSE REACTIONS

Adverse reactions reported in < 1% of subjects included application site irritation, application site pruritus, folliculitis, skin hypopigmentation, hypercalcemia, urticaria, and exacerbation of psoriasis. (6.1)

To report SUSPECTED ADVERSE REACTIONS, contact LEO Pharma Inc. at 1-877-494-4536 or FDA at 1-800-FDA-1088 or www.fda.gov/medwatch.

FULL PRESCRIBING INFORMATION

1 INDICATIONS AND USAGE

Enstilar® (calcipotriene and betamethasone dipropionate) Foam is indicated for the topical treatment of plaque psoriasis in patients 12 years and older.

2 DOSAGE AND ADMINISTRATION

Shake can prior to using Enstilar Foam. Apply Enstilar Foam to affected areas once daily for up to 4 weeks. The maximum dose should not exceed 60 grams every 4 days. Rub in Enstilar Foam gently. Wash hands after applying the product. Discontinue Enstilar Foam when control is achieved.

Enstilar Foam should not be used:

- with occlusive dressings unless directed by a healthcare provider.
- on the face, groin, or axillae, or if skin atrophy is present at the treatment site.

Enstilar Foam is not for oral, ophthalmic, or intravaginal use.

3 DOSAGE FORMS AND STRENGTHS

Enstilar Foam: 0.005%/0.064% - each gram contains 50 mcg calcipotriene and 0.643 mg of betamethasone dipropionate in a white to off-white opalescent liquid in a pressurized aluminum spray can with a continuous valve and actuator. At administration the product is a white to off-white foam after evaporation of the propellants.

4 CONTRAINDICATIONS

None.

5 WARNINGS AND PRECAUTIONS

5.1 Flammability

The propellants in Enstilar Foam are flammable. Instruct the patient to avoid fire, flame, and smoking during and immediately following application.

5.2 Hypercalcemia and Hypercalciuria

Hypercalcemia and hypercalciuria have been observed with use of Enstilar Foam. If hypercalcemia or hypercalciuria develop, discontinue treatment until parameters of calcium metabolism have normalized. The incidence of hypercalcemia and hypercalciuria following Enstilar Foam treatment of more than 56 weeks has not been evaluated [see Clinical Pharmacology (12.2)].

5.3 Effects on Endocrine System

Hypothalamic-Pituitary-Adrenal Axis Suppression

Systemic absorption of topical corticosteroids can cause reversible hypothalamic-pituitary-adrenal (HPA) axis suppression with the potential for clinical glucocorticosteroid insufficiency. This may occur during treatment or upon withdrawal of treatment. Factors that predispose a patient to HPA axis suppression include the use of high-potency steroids, large treatment surface areas, prolonged use, use of occlusive dressings, altered skin barrier, liver failure, and young age.

Evaluation for HPA axis suppression may be done by using the adrenocorticotropic hormone (ACTH) stimulation test. If HPA axis suppression is documented, gradually withdraw Enstilar Foam, reduce the frequency of application, or substitute with a less potent corticosteroid.

The following trials evaluated the effects of Enstilar Foam on HPA axis suppression [see Clinical Pharmacology (12.2)]:

- In a trial evaluating the effects of Enstilar Foam on the HPA axis, 35 adult subjects applied Enstilar Foam on the body and scalp. Adrenal suppression was not observed in any subjects after 4 weeks of treatment.
- In another trial, 33 adolescent subjects age 12 to 17 years applied Enstilar Foam on the body and scalp. Adrenal suppression occurred in 3 (9%) of the subjects.
- In a trial, 21 subjects aged 18 years and older with plaque psoriasis applied Enstilar Foam once daily for 4 weeks and then twice weekly on 2 non-consecutive days for 52 weeks, including once daily for 4 weeks if loss of response occurred. Adrenal suppression was observed in 2 (10%) of the subjects.

Cushing's Syndrome and Hyperglycemia

Systemic effects of topical corticosteroids may also include Cushing's syndrome, hyperglycemia, and glucosuria.

Additional Considerations for Endocrine Adverse Reactions

Pediatric patients may be more susceptible to systemic toxicity due to their larger skin surface to body mass ratios [see Use in Specific Populations (8.4)].

Use of more than one corticosteroid-containing product at the same time may increase the total systemic corticosteroid exposure.

5.4 Allergic Contact Dermatitis

Allergic contact dermatitis has been observed with topical calcipotriene and topical corticosteroids. Allergic contact dermatitis to a topical corticosteroid is usually diagnosed by observing a failure to heal rather than a clinical exacerbation. Corroborate such an observation with appropriate diagnostic patch testing.

5.5 Ophthalmic Adverse Reactions

Use of topical corticosteroids, including Enstilar® Foam, may increase the risk of posterior subcapsular cataracts and glaucoma. Cataracts and glaucoma have been reported with the postmarketing use of topical corticosteroid products. Avoid contact with Enstilar Foam with eyes. Enstilar Foam may cause eye irritation. Advise patients to report any visual symptoms and consider referral to an ophthalmologist for evaluation.

6 ADVERSE REACTIONS

6.1 Clinical Trials Experience

Because clinical trials are conducted under widely varying conditions, adverse reaction rates observed in the clinical trials of a drug cannot be directly compared to rates in the clinical trials of another drug and may not reflect the rates observed in practice.

Clinical Trials Conducted in Subjects 18 years and older with Psoriasis

The rates of adverse reactions described below were from three randomized, multicenter, vehicle and/or active-controlled clinical trials in adult subjects with plaque psoriasis [see Clinical Studies (14)]. Subjects applied study product once daily for 4 weeks, and the median weekly dose of Enstilar Foam was 25 grams. Adverse reactions reported in <1% of adult subjects treated with Enstilar Foam included: application site irritation, application site pruritus, folliculitis, skin hypopigmentation, hypercalcemia, urticaria, and exacerbation of psoriasis.

Clinical Trials Conducted in Subjects 12 to 17 years with Psoriasis

In one uncontrolled clinical trial, 106 subjects aged 12 to 17 years with plaque psoriasis of the scalp and body applied Enstilar Foam once daily for up to 4 weeks. The median weekly dose was 40 grams. Adverse reactions reported in <1% of adolescent subjects treated were acne, erythema, application site pain, and skin reactions [see Use in Specific Populations (8.4) and Clinical Pharmacology (12.2)].

6.2 Postmarketing Experience

Because adverse reactions are reported voluntarily from a population of uncertain size, it is not always possible to reliably estimate their frequency or establish a causal relationship to drug exposure.

Postmarketing reports for local adverse reactions to Enstilar Foam included application site burning.

Postmarketing reports for local adverse reactions to topical corticosteroids included atrophy, striae, telangiectasia, dryness, perioral dermatitis, secondary infection, and miliaria.

Ophthalmic adverse reactions of cataracts, glaucoma, and increased intraocular pressure have been reported with the use of topical corticosteroids, including topical betamethasone products.

8 USE IN SPECIFIC POPULATIONS

8.1 Pregnancy

Risk Summary

Available data with Enstilar Foam are not sufficient to evaluate a drug-associated risk for major birth defects, miscarriages, or adverse maternal or fetal outcomes. Although there are no available data on use of the calcipotriene component in pregnant women, systemic exposure to calcipotriene after topical administration of Enstilar Foam is likely to be low [see Clinical Pharmacology (12.3)].

Observational studies suggest an increased risk of having low birth weight infants with the maternal use of potent or super potent topical corticosteroids (see Data). Advise pregnant women that Enstilar® Foam may increase the potential risk of having a low birth weight infant and to use Enstilar Foam on the smallest area of skin and for the shortest duration possible.

In animal reproduction studies, oral administration of calcipotriene to pregnant rats during the period of organogenesis resulted in an increased incidence of minor skeletal abnormalities, including enlarged fontanelles and extra ribs (see Data). Oral administration of calcipotriene to pregnant rabbits during the period of organogenesis had no apparent effects on embryo-fetal development. Subcutaneous administration of betamethasone dipropionate to pregnant rats and rabbits during the period of organogenesis resulted in fetal toxicity, including fetal deaths, reduced fetal weight, and fetal malformations (cleft palate and crooked or short tail) (see Data). The available data do not allow the calculation of relevant comparisons between the systemic exposures of calcipotriene and betamethasone dipropionate observed in animal studies to the systemic exposures that would be expected in humans after topical use of Enstilar Foam.

The background risk of major birth defects and miscarriage in the indicated population is unknown. All pregnancies have a background risk of birth defect, loss, or other adverse outcomes. In the U.S. general population, the estimated background risk of major birth defects and miscarriage in clinically recognized pregnancies is 2% to 4% and 15% to 20%, respectively.

Data

Human Data

Available observational studies in pregnant women did not identify a drug-associated risk of major birth defects, preterm delivery, or fetal mortality with the use of topical corticosteroids of any potency. However, when the dispensed amount of potent or super potent topical corticosteroids exceeded 300 grams during the entire pregnancy, maternal use was associated with an increased risk of low birth weight in infants.

Animal Data

Embryo-fetal development studies with calcipotriene were performed by the oral route in rats and rabbits. Pregnant rats received dosages of 0, 6, 18, or 54 mcg/kg/day (0, 36, 108, and 324 mcg/m^2/day, respectively) on days 6-15 of gestation (the period of organogenesis). There were no apparent effects on maternal survival, behavior, or body weight gain, no effects on litter parameters, and no effects on the incidence of major malformations in fetuses. Fetuses from dams dosed at 54 mcg/kg/day exhibited a significantly increased incidence of minor skeletal abnormalities, including enlarged fontanelles and extra ribs.

Pregnant rabbits were dosed daily with calcipotriene at exposures of 0, 4, 12, or 36 mcg/kg/day (0, 48, 144, and 432 mcg/m^2/day, respectively) on days 6-18 of gestation (the period of organogenesis). Mean maternal body weight gain was reduced in animals dosed at 12 or 36 mcg/kg/day. The incidence of fetal deaths was increased in the group dosed at 36 mcg/kg/day; reduced fetal weight was also observed in this group. The incidence of major malformations among fetuses was not affected. An increase in the incidence of minor skeletal abnormalities, including incomplete ossification of sternebrae, pubic bones, and forelimb phalanges, was observed in the group dosed at 36 mcg/kg/day.

Embryo-fetal development studies with betamethasone dipropionate were performed via subcutaneous injection in mice and rabbits. Pregnant mice were administered doses of 0, 156, 625, or 2500 mcg/kg/day (0, 468, 1875, and 7500 mcg/m^2/day, respectively) on days 7 through 13 of gestation (the period of organogenesis). Betamethasone dipropionate induced fetal toxicity, including fetal deaths, reduced fetal weight, malformations (increased incidence of the cleft palate and crooked or short tail), and minor skeletal abnormalities (delayed ossification of vertebra and sternebrae). Fetal toxicity was observed at the lowest exposure that was evaluated (156 mcg/kg/day).

Pregnant rabbits were injected subcutaneously at dosages of 0, 0.625, 2.5, and 10 mcg/kg/day (0, 7.5, 30, and 120 mcg/m^2/day, respectively) on days 6 through 18 of gestation (the period of organogenesis). Betamethasone dipropionate induced fetal toxicity, including fetal deaths, reduced fetal weight, external malformations (including malformed ears, cleft palate, umbilical hernia, kinked tail, club foot, and club hand), and skeletal malformations (including absence of phalanges of the first digit and cranial dysplasia) at dosages of 2.5 mcg/kg/day and above.

Calcipotriene was evaluated for effects on peri- and post-natal development when orally administered to pregnant rats at dosages of 0, 6, 18 or 54 mcg/kg/day (0, 36, 108, and 324 mcg/m^2/day, respectively) from gestation day 15 through day 20 postpartum. No remarkable effects were observed on any parameter, including survival, behavior, body weight, litter parameters, or the ability to nurse or rear pups.

Betamethasone dipropionate was evaluated for effects on peri- and post-natal development when orally administered to pregnant rats at dosages of 0, 100, 300, and 1000 mcg/kg/day (0, 600, 1800, and 6000 mcg/m^2/day, respectively) from gestation day 6 through day 20 postpartum. Mean maternal body weight was significantly reduced on gestation day 20 in animals dosed at 300 and 1000 mcg/kg/day. The mean duration of gestation was slightly, but statistically significantly, increased at 100, 300, and 1000 mcg/kg/day. The mean percentage of pups that survived to day 4 was reduced in relation to dosage. On lactation day 5, the percentage of pups with a reflex to right themselves when placed on their back was significantly reduced at 1000 mcg/kg/day. No effects on the ability of pups to learn were observed, and the ability of the offspring of treated rats to reproduce was not affected.

8.2 Lactation

Risk Summary

There is no information regarding the presence of topically administered calcipotriene and betamethasone dipropionate in human milk, the effects on the breastfed infant, or the effects on milk production. Concentrations of calcipotriene in plasma are low after topical administration, and therefore, concentrations in human milk are likely to be low [see Clinical Pharmacology (12.3)]. It is not known whether topical administration of large amounts of betamethasone dipropionate could result in sufficient systemic absorption to produce detectable quantities in human milk. The developmental and health benefits of breastfeeding should be considered along with the mother's clinical need for Enstilar® Foam and any potential adverse effects on the breastfed child from Enstilar Foam or from the underlying maternal condition.

Clinical Considerations

To minimize potential exposure to the breastfed infant via breast milk, use Enstilar Foam on the smallest area of skin and for the shortest duration possible while breastfeeding. Advise breastfeeding women not to apply Enstilar Foam directly to the nipple and areola to avoid direct infant exposure [see Use in Specific Populations (8.4)].

8.4 Pediatric Use

The safety and effectiveness of Enstilar Foam for the treatment of mild to severe plaque psoriasis have been established in pediatric patients age 12 to 17 years. The use of Enstilar Foam for this indication is supported by evidence from adequate and well-controlled trials in adults and from one uncontrolled trial in 106 adolescents age 12 to 17 years with psoriasis of the body and scalp. Calcium metabolism was evaluated in all pediatric subjects and no cases of hypercalcemia or clinically relevant changes in urinary calcium were reported. Hypothalamic pituitary adrenal (HPA) axis suppression was evaluated in a subset of 33 pediatric subjects with moderate plaque psoriasis of the body and scalp (mean body surface area involvement of 16% and mean scalp area involvement of 56%). After 4 weeks of once daily treatment with a mean weekly dose of 47 grams, HPA axis suppression was observed in 3 of 33 subjects (9%) [see Warnings and Precautions (5.2), Adverse Reactions (6.1) and Clinical Pharmacology (12.2)].

Because of a higher ratio of skin surface area to body mass, children under the age of 12 years are at particular risk of systemic adverse effects when they are treated with topical corticosteroids. Pediatric patients are, therefore, also at greater risk of HPA axis suppression and adrenal insufficiency with the use of topical corticosteroids including Enstilar Foam [see Warnings and Precautions (5.3) and Clinical Pharmacology (12.2)].

Cushing's syndrome, linear growth retardation, delayed weight gain, and intracranial hypertension have been reported in pediatric patients treated with topical corticosteroids.

Local adverse reactions including striae have been reported with use of topical corticosteroids in pediatric patients.

The safety and effectiveness of Enstilar Foam in pediatric patients less than 12 years of age have not been established.

8.5 Geriatric Use

Of the total number of subjects in the controlled clinical studies of Enstilar Foam, 97 subjects were 65 years and over, and 21 were 75 and over.

No overall differences in safety or effectiveness of Enstilar Foam were observed between these subjects and younger subjects, and other reported clinical experience has not identified differences in responses between the elderly and younger patients, but greater sensitivity of some older individuals cannot be ruled out.

11 DESCRIPTION

Enstilar Foam contains calcipotriene hydrate and betamethasone dipropionate. It is for topical use only.

Calcipotriene Hydrate

Calcipotriene hydrate is a synthetic vitamin D analog and has the chemical name 9,10-secochola-5,7,10(19),22-tetraene-1,3,24-triol,24-cyclo-propyl-,monohydrate, (1α,3β,5Z,7E,22E,24S) with the empirical formula C27H40O3∙H2O), a molecular weight of 430.6, and the following structural formula (calcipotriene hydrate is a white to almost white, crystalline compound):

Betamethasone Dipropionate

Betamethasone dipropionate is a synthetic corticosteroid and has the chemical name pregna-1,4-diene-3,20-dione-9-fluoro-11-hydroxy-16-methyl-17,21-bis(1-oxypropoxy)-(11β,16β), with the empirical formula C28H37FO7, a molecular weight of 504.6, and the following structural formula (betamethasone dipropionate is a white to almost white, crystalline powder):

Enstilar® Foam

Each gram of Enstilar Foam contains 50 mcg of calcipotriene (equivalent to 52.2 mcg of calcipotriene hydrate) and 0.643 mg of betamethasone dipropionate (equivalent to 0.5 mg of betamethasone) in a base of white petrolatum, polyoxypropylene stearyl ether, mineral oil, all-rac-alpha-tocopherol, and butylhydroxytoluene. Enstilar Foam is a white to off-white opalescent liquid in a pressurized aluminum spray can with a continuous valve and actuator. The propellants used in Enstilar Foam are dimethyl ether and butane. At administration, the product is a white to off-white foam after evaporation of the propellants. Enstilar Foam has the appearance of a non-expanding foam that gradually collapses after spraying.

12 CLINICAL PHARMACOLOGY

12.1 Mechanism of Action

Enstilar Foam combines the pharmacological effects of calcipotriene hydrate as a synthetic vitamin D3 analog and betamethasone dipropionate as a synthetic corticosteroid. However, while their pharmacologic and clinical effects are known, the exact mechanisms of their actions in the treatment of plaque psoriasis are unknown.

12.2 Pharmacodynamics

Hypothalamic-Pituitary-Adrenal (HPA) Axis Suppression:

HPA axis suppression as indicated by a 30-minute post-stimulation cortisol level of ≤18 mcg/dL was evaluated in the following trials [see Warnings and Precautions (5.3)]:

- Enstilar Foam was applied to adult subjects (N=35) with moderate to severe plaque psoriasis affecting a mean body surface area of 18% (range 12 to 28%) and mean scalp area of 50 % (range 30 to 100%). The mean ± SD weekly dose used was 62 ± 28 grams. HPA axis suppression was not observed in any subjects after 4 weeks of treatment. Lack of adrenal suppression observed in this trial does not rule out the risk of HPA axis suppression.
- Enstilar Foam was applied to adolescent subjects (N=33) age 12 to 17 years with moderate plaque psoriasis affecting a mean body surface area of 16% (range from 10% to 21%) and mean scalp area of 56% (range from 25% to 90%). The mean ± SD weekly dose used was 47 ± 22 grams. HPA axis suppression was observed in 3 (9%) of the subjects.
- Enstilar® Foam was applied once daily for 4 weeks to adult subjects (N=21) with plaque psoriasis affecting a mean body surface area of 15% (range 10 to 30%), then twice weekly on 2 non-consecutive days for 52 weeks with 4 weeks and once daily treatment was resumed if loss of response occurred. The mean ± SD total dose used in the 52-week period was 1400 ± 905 grams (including total dose of 528 ± 650 grams used in the loss of response period). HPA axis suppression was observed in 2 (10%) of the subjects at Week 56.

Effects on Calcium Metabolism

- Effects of once daily application of Enstilar Foam for 4 weeks on calcium metabolism in adult subjects (N=564) with plaque psoriasis were examined in three randomized, multicenter, vehicle- and/or active-controlled clinical trials. Following once daily application of Enstilar Foam, elevated serum calcium levels outside the normal range were observed in 3 subjects. Elevated urinary calcium levels outside the normal range were observed in 17 subjects.
- In a trial, calcium metabolism was evaluated in 106 adolescent subjects aged 12 to 17 years with plaque psoriasis of the scalp and body after once daily application of Enstilar Foam for 4 weeks. No cases of hypercalcemia and no clinically relevant changes in urinary calcium were reported.
- In a trial, 272 subjects aged 18 years and older with plaque psoriasis applied Enstilar Foam once daily for 4 weeks and then twice weekly on 2 non-consecutive days for 52 weeks, including once daily for 4 weeks if loss of response occurred. No cases of hypercalcemia and no clinically relevant changes in urinary calcium were reported.

Vasoconstrictor Assay

Enstilar Foam is in the mid to potent range corticosteroid as demonstrated by studies in healthy subjects when compared with other topical corticosteroids. However, similar blanching scores do not necessarily imply therapeutic equivalence.

12.3 Pharmacokinetics

Absorption

The PK of Enstilar Foam was investigated in both adults (N = 35) and a subset of pediatric subjects with plaque psoriasis age 12 to 17 years (N=33) following once daily application of Enstilar Foam on the body and scalp for 4 weeks.

Enstilar Foam was applied to adult subjects with moderate to severe plaque psoriasis affecting a mean body surface area of 18% and mean scalp area of 50%. Following application of a mean ± SD weekly dose of 62 ± 28 grams of Enstilar Foam, calcipotriene was quantifiable in 1 of 35 (3%) subjects and its main metabolite, MC1080, in 3 of 35 (9%) subjects. For subjects with measurable concentrations, the maximal plasma concentrations (Cmax) and area under the concentration curve until the last measured time point (AUClast) for calcipotriene were 55.9 pg/mL and 82.5 pg*h/mL, respectively; and the mean ± SD Cmax and AUClast for MC1080 was 24.4 ± 1.9 pg/mL and 59.3 ± 5.4 pg*h/mL, respectively. Betamethasone dipropionate was quantifiable in 5 of 35 (14%) subjects and its main metabolite, betamethasone 17-propionate (B17P), was quantifiable in 27 of 35 (77%) subjects. The mean ± SD Cmax and AUClast for betamethasone dipropionate were 52.2 ± 19.7 pg/mL and 36.5 ± 27.4 pg*h/mL, respectively and for B17P were 147.9 ± 224.0 pg/mL and 683.6 ± 910.6 pg*h/mL, respectively.

Enstilar Foam was applied to pediatric subjects age 12 to 17 years with moderate plaque psoriasis affecting a mean body surface area of 16% and mean scalp area of 56%. Following application of a mean ± SD weekly dose of 47 ± 22 grams of Enstilar Foam, calcipotriene and its metabolite MC1080 were below the lower limit of quantification in all plasma samples. Betamethasone dipropionate was quantifiable in 12 of 33 (36%) subjects with the Cmax ranging from 31.1-480 pg/mL. The metabolite of betamethasone 17-propionate (B17P) was quantifiable in 6 of 33 (18%) subjects with the Cmax ranging from 30.8–91.7 pg/mL.

Elimination

Metabolism

Calcipotriene: Calcipotriene metabolism following systemic uptake is rapid and occurs in the liver. The primary metabolites of calcipotriene are less potent than the parent compound.

Calcipotriene is metabolized to MC1046 (the α,β-unsaturated ketone analog of calcipotriene), which is metabolized further to MC1080 (a saturated ketone analog). MC1080 is the major metabolite in plasma. MC1080 is slowly metabolized to calcitroic acid.

Betamethasone dipropionate: Betamethasone dipropionate is metabolized to betamethasone 17-propionate (B17P) and betamethasone, including the 6β-hydroxy derivatives of those compounds by hydrolysis. Betamethasone 17-propionate (B17P) is the primary metabolite.

13 NONCLINICAL TOXICOLOGY

13.1 Carcinogenesis, Mutagenesis, Impairment of Fertility

When calcipotriene was applied topically to mice for up to 24 months at dosages of 3, 10, and 30 mcg/kg/day (9, 30, and 90 mcg/m^2/day, respectively), no significant changes in tumor incidence were observed when compared to control.

A 104-week oral carcinogenicity study was conducted with calcipotriene in male and female rats at doses of 1, 5, and 15 mcg/kg/day (6, 30, and 90 mcg/m^2/day, respectively). Beginning week 71, the dosage for high-dose animals of both genders was reduced to 10 mcg/kg/day (60 mcg/m^2/day). A treatment-related increase in benign C-cell adenomas was observed in the thyroid of females that received 15 mcg/kg/day. A treatment-related increase in benign pheochromocytomas was observed in the adrenal glands of males that received 15 mcg/kg/day. No other statistically significant differences in tumor incidence were observed when compared to control. The relevance of these findings to patients is unknown.

When betamethasone dipropionate was applied topically to CD-1 mice for up to 24 months at dosages approximating 1.3, 4.2, and 8.5 mcg/kg/day in females, and 1.3, 4.2, and 12.9 mcg/kg/day in males (up to 26 mcg/m^2/day and 39 mcg/m^2/day, in females and males, respectively), no significant changes in tumor incidence were observed when compared to control.

When betamethasone dipropionate was administered via oral gavage to male and female Sprague Dawley rats for up to 24 months at dosages of 20, 60, and 200 mcg/kg/day (120, 360, and 1200 mcg/m^2/day, respectively), no significant changes in tumor incidence were observed when compared to control.

Calcipotriene did not elicit any genotoxic effects in the Ames mutagenicity assay, the mouse lymphoma TK locus assay, the human lymphocyte chromosome aberration test, or the mouse micronucleus test. Betamethasone dipropionate did not elicit any genotoxic effects in the Ames mutagenicity assay, the mouse lymphoma TK locus assay, or in the rat micronucleus test.

Studies in rats with oral doses of up to 54 mcg/kg/day (324 mcg/m^2/day) of calcipotriene indicated no impairment of fertility or general reproductive performance. Studies in male rats at oral doses of up to 200 mcg/kg/day (1200 mcg/m^2/day), and in female rats at oral doses of up to 1000 mcg/kg/day (6000 mcg/m^2/day), of betamethasone dipropionate indicated no impairment of fertility.

14 CLINICAL STUDIES

Two multicenter, randomized, double-blind trials were conducted in adult subjects with plaque psoriasis.

- In Trial One, 302 subjects were randomized to 1 of 3 treatment groups: Enstilar® Foam, betamethasone dipropionate in the same vehicle, or calcipotriene in the same vehicle.
- In Trial Two, 426 subjects were randomized to one of two treatment groups: Enstilar Foam or the vehicle alone. Baseline disease severity was graded using a 5-point Investigator's Global Assessment (IGA). At baseline subjects scored "Mild", "Moderate", or "Severe". The majority of subjects in both trials (76% and 75%) had disease of "Moderate" severity at baseline, 14% and 15% of subjects had disease of "Mild" severity at baseline and 10% of subjects had "Severe" disease at baseline in both trials. The extent of disease involvement assessed by mean body surface area was 7.1% (range 2 to 28%) and 7.5% (range 2 to 30%). In both trials, subjects were treated once daily for up to 4 weeks.

Efficacy was assessed with treatment success defined as the proportion of subjects at Week 4 who were "Clear" or "Almost Clear" according to the IGA. Subjects with "Mild" disease at baseline were required to be "Clear" to be considered a treatment success. Table 1 presents the efficacy results for these trials.

Table 1. Percentage of Subjects Achieving Treatment Success According to the Investigator's Global Assessment of Disease Severity [Subjects with "Mild" disease at baseline were required to be "Clear" to be considered a treatment success.]
 | Enstilar Foam | Betamethasone dipropionate in vehicle | Calcipotriene in vehicle | Vehicle
Trial One Week 4 | (N=100) 45.0% | (N=101) 30.7% | (N=101) 14.9% | - -
Trial Two Week 4 | (N=323) 53.3% | - - | - - | (N=103) 4.8%

Long-term Use

A randomized, double-blind, vehicle-controlled trial (NCT02899962) evaluated the long-term use of Enstilar Foam in subjects who achieved treatment success (defined as IGA score of "Clear" or "Almost Clear" with at least a 2 grade improvement from baseline) after an initial 4-week treatment with once daily Enstilar Foam. These subjects (N=521) were randomized to receive Enstilar Foam or vehicle foam twice weekly on 2 non-consecutive days for up to 52 additional weeks. Subjects experiencing loss of response (defined as an IGA score of at least "Mild") were treated once daily with Enstilar® Foam for 4 weeks, and those who regained an IGA score of "Clear" or "Almost Clear" after 4 weeks then continued randomized treatment. Disease severity was graded using a 5-point IGA. The majority of subjects in this trial (82%) had disease of "Moderate" severity at baseline, 11% of subjects had disease of "Mild" severity at baseline, and 7% of subjects had "Severe" disease at baseline. The extent of disease involvement assessed by mean body surface area was 8.3% (range 1 to 38%) at baseline.

The median time to loss of response was 56 days for subjects treated with Enstilar Foam twice weekly compared to 30 days for subjects treated with vehicle foam twice weekly. Over the 52-week assessment period, subjects in the Enstilar Foam twice weekly group experienced loss of response a median of 2.0 times compared to 3.0 times for subjects in the vehicle foam twice weekly group. Figure 1 presents the percentage of subjects maintaining an IGA score of "Clear" or "Almost Clear" through Week 52 after randomization.

Figure 1: Percentage of Subjects Maintaining an IGA Score of "Clear" or "Almost Clear" Through Week 52 After Randomization

16 HOW SUPPLIED/STORAGE AND HANDLING

16.1 How Supplied

Enstilar (calcipotriene and betamethasone dipropionate) Foam, 0.005%/0.064% is a white to off-white opalescent liquid in a pressurized aluminum spray can with a continuous valve and actuator. At administration, the product is a white to off-white foam after evaporation of the propellants. It is available as:

- 60 gram can (NDC 50222-302-60)
- 120 gram (2 cans of 60 gram) (NDC 50222-302-66)

16.2 Storage

- Store Enstilar Foam at 20°C - 25°C (68°F - 77°F); excursions permitted between 15°C - 30°C (59°F - 86°F). [See USP controlled room temperature].
- Contents under pressure. Do not puncture or incinerate. Do not expose to heat or store at temperatures above 120°F (49°C). Do not freeze.
- Unused product should be discarded six months after the can has been opened.
- Keep out of the reach of children.

16.3 Handling

- Enstilar Foam is flammable; avoid heat, flame or smoking when using this product.

17 PATIENT COUNSELING INFORMATION

See FDA-approved patient labeling (Patient Information and Instructions for Use).

Flammability

Instruct patients that Enstilar Foam is flammable; avoid heat, flame, or smoking when applying this medication.

Administration Instructions

- Shake before use and spray the foam by holding the can in any orientation except horizontally.
- Gently rub in Enstilar Foam to your affected areas.
- Do not use more than 60 grams every 4 days.
- Discontinue therapy when control is achieved unless directed otherwise by the healthcare provider.
- Avoid use of Enstilar Foam on the face, underarms, groin or eyes. If this medicine gets on face or in mouth or eyes, wash area right away.
- Do not occlude the treatment area with a bandage or other covering unless directed by the healthcare provider. Instruct the patients not to use other products containing calcipotriene or a corticosteroid with Enstilar Foam without first talking to the healthcare provider.
- Wash hands after application.

Local Reactions and Skin Atrophy

Advise patients that local reactions and skin atrophy are more likely to occur with occlusive use, prolonged use or use of higher potency corticosteroids.

Hypercalcemia and Hypercalciuria

Advise patients that hypercalcemia and hypercalciuria have been observed with the use of Enstilar Foam [see Warnings and Precautions (5.2)].

HPA Axis Suppression, Cushing's Syndrome, and Hyperglycemia

Advise patients that Enstilar Foam can cause HPA axis suppression, Cushing's syndrome, and/or hyperglycemia [see Warnings and Precautions (5.3)].

Ophthalmic Adverse Reactions

Advise patients to avoid contact of Enstilar Foam with eyes and to report any visual symptoms [see Warnings and Precautions (5.5)].

Pregnancy and Lactation

- Advise pregnant women that Enstilar Foam may increase the potential risk of having a low birth weight infant and to use Enstilar Foam on the smallest area of skin and for the shortest duration possible [see Use in Specific Populations (8.1)].
- Advise breastfeeding women not to apply Enstilar Foam directly to the nipple and areola to avoid direct infant exposure [see Use in Specific Populations (8.2)].

Manufactured by: LEO Laboratories Ltd., 285 Cashel Road, Dublin 12, Ireland

Distributed by: LEO Pharma Inc., Madison, NJ 07940, USA

Enstilar® is a registered trademark of LEO Pharma A/S.
© 2022, LEO Pharma Inc. All rights reserved.

PATIENT INFORMATION
ENSTILAR® [EN-still-ar]
(calcipotriene and betamethasone dipropionate)
Foam

Important: Enstilar Foam is for use on skin only (topical). Do not get Enstilar Foam near or in your mouth, eyes, or vagina.

There are other medicines that contain the same medicine that is in Enstilar Foam and are used to treat plaque psoriasis. Do not use other products containing calcipotriene or a corticosteroid medicine with Enstilar Foam without talking to your healthcare provider first.

What is Enstilar Foam?
Enstilar Foam is a prescription medicine used on the skin (topical) to treat plaque psoriasis in people 12 years of age and older.
It is not known if Enstilar Foam is safe and effective in children under 12 years of age.

Before you use Enstilar Foam, tell your healthcare provider about all of your medical conditions, including if you:

- have a calcium metabolism disorder.
- Have thinning skin (atrophy) at the treatment site
- are pregnant or plan to become pregnant. It is not known if Enstilar Foam will harm your unborn baby. Enstilar Foam may increase your chance of having a low birth weight baby. If you use Enstilar Foam during pregnancy, use Enstilar Foam on the smallest area of the skin and for the shortest time needed.
- are breastfeeding or plan to breastfeed. It is not known if Enstilar Foam passes into your breast milk. Breastfeeding women should use Enstilar Foam on the smallest area of the skin and for the shortest time needed. Do not apply Enstilar Foam directly to your nipple and areola to avoid contact with your baby.

Tell your healthcare provider about all the medicines you take, including prescription and over-the-counter medicines, vitamins and herbal supplements.

How should I use Enstilar Foam?
See the "Instructions for Use" for detailed information about the right way to use Enstilar Foam.

- Use Enstilar Foam exactly as your healthcare provider tells you to use it.
- Your healthcare provider should tell you how much Enstilar Foam to use and where to use it.
- Apply Enstilar Foam to the affected areas of your skin 1 time a day for up to 4 weeks. You should stop treatment when your plaque psoriasis is under control unless your healthcare provider gives you other instructions.
- Do not use more than 60 grams of Enstilar Foam every 4 days.
- Do not use Enstilar Foam longer than prescribed. Using too much Enstilar Foam, or using it too often, or for too long can increase your risk for having serious side effects.
- Shake the Enstilar Foam can before you use it.
- Gently rub in Enstilar Foam to your affected areas.
- Avoid using Enstilar Foam on your face, groin, or armpits, or if you have thinning of your skin (atrophy) at the treatment site.
- If you accidentally get Enstilar Foam on your face, in your mouth or in your eyes, wash the area with water right away.
- Wash your hands after using Enstilar Foam unless you are using the medicine to treat your hands.
- Do not bandage or cover the treated skin area, unless instructed by your healthcare provider.

What should I avoid while using Enstilar Foam?
Enstilar Foam is flammable. Avoid fire, flame, and smoking when applying and right after you apply Enstilar Foam.

What are the possible side effects of Enstilar Foam?
Enstilar Foam may cause serious side effects, including:

- Too much calcium in your blood or urine. Your healthcare provider may tell you to stop or temporarily stop treatment with Enstilar Foam if you have too much calcium in your blood or urine. Your healthcare provider may do blood and urine tests to check your calcium levels and adrenal gland function while you are using Enstilar Foam.
- Enstilar® Foam can pass through your skin. Too much Enstilar Foam passing through your skin can cause your adrenal glands to stop working properly. Your healthcare provider may do blood tests to check for adrenal gland problems. Your healthcare provider may tell you to stop or temporarily stop treatment with Enstilar Foam.
- Cushing's syndrome, a condition that happens when your body is exposed to too much of the hormone cortisol.
- High blood sugar (hyperglycemia) and sugar in your urine
- Skin problems, including reactions where Enstilar Foam is applied, and allergic reactions (allergic contact dermatitis). Tell your healthcare provider if you have any skin problems, including:

- thinning of your skin
- burning
- inflammation
- itiching
- irritation

- dryness
- changes in skin color
- redness
- infection
- raised bumps on your skin

- Eye problems. Using Enstilar Foam may increase your chance of getting cataracts and glaucoma. Do not get Enstilar Foam in your eyes because it may cause eye irritation. Tell your healthcare provider if you have blurred vision or other vision problems during treatment with Enstilar Foam.

The most common side effects of Enstilar Foam include:

- irritation
- itching
- inflamed hair pores (folliculitis)

- changes in skin color
- rash with raised red bumps or skin welts (hives)
- worsening of your psoriasis

These are not all the possible side effects of Enstilar Foam.

Call your doctor for medical advice about side effects. You may report side effects to FDA at 1-800-FDA-1088.

How should I store Enstilar Foam?

- Store Enstilar Foam at room temperature between 68°F to 77°F (20°C to 25°C).
- Do not expose Enstilar Foam to heat or store at temperatures above 120°F (49°C).
- Do not puncture or burn the Enstilar Foam can.
- Do not freeze Enstilar Foam.
- Enstilar Foam has an expiration date (exp.) marked on the can. Do not use after this date.
- Throw away (dispose of) unused Enstilar Foam 6 months after the can has been opened.

Keep Enstilar Foam and all medicines out of the reach of children.

General information about the safe and effective use of Enstilar Foam.
Medicines are sometimes prescribed for purposes other than those listed in a Patient Information leaflet. Do not use Enstilar Foam for a condition for which it was not prescribed. Do not give Enstilar Foam to other people, even if they have the same symptoms you have. It may harm them. You can ask your pharmacist or healthcare provider for information about Enstilar Foam that is written for health professionals.

What are the ingredients in Enstilar Foam?
Active ingredients: calcipotriene and betamethasone dipropionate.
Inactive ingredients: white petrolatum, polyoxypropylene stearyl ether, mineral oil, all-rac-alpha-tocopherol, and butylhydroxytoluene.
Propellants: dimethyl ether and butane.
Manufactured by: LEO Laboratories Ltd., 285 Cashel Road, Dublin 12, Ireland
Distributed by: LEO Pharma Inc., Madison, NJ 07940, USA
Enstilar® is a registered trademark of LEO Pharma A/S.
© 2022, LEO Pharma Inc. All rights reserved.

This Patient Information has been approved by the U.S. Food and Drug Administration.

Revised: 4/2022

INSTRUCTIONS FOR USE ENSTILAR® [EN-still-ar] (calcipotriene and betamethasone dipropionate) Foam

This Instructions for Use contains information on how to apply Enstilar Foam.

Important Information You Need to Know Before Applying Enstilar Foam: Enstilar Foam is for use on skin only (topical). Do not get Enstilar Foam near or in your mouth, eyes or vagina. If you accidentally get Enstilar Foam on the face, in the mouth or in the eyes, wash the area with water right away. Do not swallow Enstilar Foam.

Applying Enstilar Foam:

Follow your healthcare provider's instructions on how much Enstilar Foam to use and where to use it.

Wash your hands before applying Enstilar Foam.
Step 1: Remove the cap from the can. Shake the can before use.

Step 2: Hold the can at least 1.5 inches from the affected area.

Step 3: The foam can be sprayed holding the can in any position except sideways (horizontally).
To spray, push down on the nozzle.
Note: Enstilar Foam will slowly become smaller in size after spraying.

Step 4: Gently rub in Enstilar Foam into your affected skin area.
Repeat the steps above to apply Enstilar Foam to other affected areas as instructed by your healthcare provider.

Step 5: After applying Enstilar Foam, put the cap back on the can.

Step 6: Wash your hands after using Enstilar Foam unless you are using the medicine to treat your hands.

Storing Enstilar Foam

- Store Enstilar Foam at room temperature between 68°F to 77°F (20°C to 25°C).
- Do not expose Enstilar Foam to heat or store at temperatures above 120°F (49°C).
- Do not puncture or burn the Enstilar Foam can.
- Do not freeze Enstilar Foam.

Disposing of Enstilar Foam

- Enstilar Foam has an expiration date (exp.) marked on the can. Do not use after this date.
- Throw away (dispose of) unused Enstilar Foam 6 months after the can has been opened.

Keep Enstilar Foam and all medicines out of the reach of children.

Manufactured by:
LEO Laboratories Ltd.
285 Cashel Road
Dublin 12, Ireland

Distributed by:
LEO Pharma Inc.
Madison, NJ 07940, USA

Enstilar® is a registered trademark of LEO Pharma A/S.
© 2022, LEO Pharma Inc. All rights reserved.

This Instructions for Use has been approved by the U.S. Food and Drug Administration.
Revised: 4/2022

PRINCIPAL DISPLAY PANEL - 60 gram Can Carton

NDC 50222-302-60

Rx only

Enstilar®
(calcipotriene and
betamethasone
dipropionate)
Foam, 0.005%/0.064%

Shake before Use

For Topical Use Only

Not for oral, ophthalmic,
or intravaginal use

Net Wt.
60 gram

LEO®

PRINCIPAL DISPLAY PANEL - 120 gram Can Carton

NDC 50222-302-66
Rx only

Enstilar®
(calcipotriene and betamethasone
dipropionate)
Foam, 0.005%/0.064%

Shake before Use

For Topical Use Only

Not for oral, ophthalmic, or intravaginal use

Net Wt. 120 gram
(2 cans of 60 gram)

LEO®